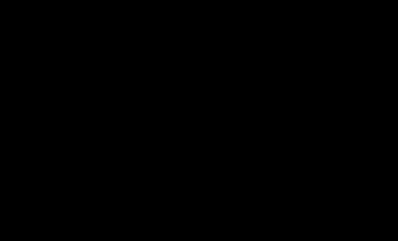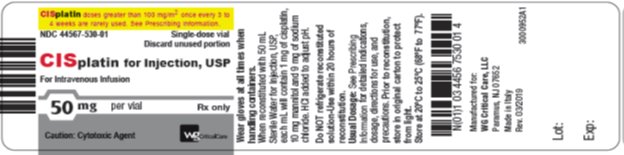 DRUG LABEL: Cisplatin
NDC: 44567-530 | Form: INJECTION, POWDER, LYOPHILIZED, FOR SOLUTION
Manufacturer: WG Critical Care, LLC
Category: prescription | Type: HUMAN PRESCRIPTION DRUG LABEL
Date: 20210927

ACTIVE INGREDIENTS: cisplatin 1 mg/1 mL
INACTIVE INGREDIENTS: Sodium Chloride; Mannitol; HYDROCHLORIC ACID

HIGHLIGHTS OF PRESCRIBING INFORMATION

These highlights do not include all the information needed to use CISPLATIN INJECTION safely and effectively. See full prescribing information for CISPLATIN INJECTION.
CISPLATIN for injection, for intravenous use Initial U.S. Approval: 1978

WARNING: NEPHROTOXICITY, PERIPHERAL NEUROPATHY, NAUSEA AND VOMITING and MYELOSUPPRESSION.

See full prescribing information for complete boxed warning.

- Nephrotoxicity: cisplatin for injection can cause severe renal toxicity, including acute renal failure. Ensure adequate hydration. Consider dose reductions or alternative treatments in patients with renal impairment. (2.1, 5.1)
- Peripheral Neuropathy: cisplatin for injection can cause dose-related peripheral neuropathy. (5.2)
- Nausea and Vomiting: cisplatin for injection can cause severe nausea and vomiting. Premedicate with antiemetics. (2.1, 5.3)
- Myelosuppression: cisplatin for injection can cause severe myelosuppression with fatalities due to infections. Monitor blood counts and interrupt therapy accordingly. (5.4)

1 INDICATIONS AND USAGE

Cisplatin for injection is a platinum-based drug indicated for the treatment of:

• Advanced testicular cancer (1.1)

• Advanced ovarian cancer (1.2)

• Advanced bladder cancer (1.3)

2 DOSAGE AND ADMINISTRATION

• Administer pre-treatment hydration and pre- and post-treatment antiemetics. (2.1)

• Cisplatin for injection has been administered intravenously at:

o Advanced testicular cancer: 20 mg/m^2 daily for 5 days per cycle (2.2)
o Advanced ovarian cancer: 75 mg/m^2 to 100 mg/m^2 per cycle once every 3 to 4 weeks (2.3)
o Advanced bladder cancer: 50 mg/m^2 to 70 mg/m^2 intravenously per cycle once every 3 to 4 weeks (2.4)
Refer to current treatment guidelines for specific dosing information.

• Administer by slow intravenous infusion. Avoid contact of cisplatin for injection with aluminum parts. (2.6)

3 DOSAGE FORMS AND STRENGTHS

Lyophilized powder: Single-dose vials containing 50 mg (3)

4 CONTRAINDICATIONS

Severe hypersensitivity to cisplatin (4)

5 WARNINGS AND PRECAUTIONS

- Hypersensitivity reactions: Anaphylaxis and death may occur; monitor for and treat accordingly (5.5)
- Ototoxicity: Cumulative toxicity may be severe particularly in pediatric patients; consider audiometric and vestibular function monitoring (5.6, 8.4)
- Ocular toxicity: Optic neuritis, papilledema, and cortical blindness may occur (5.7)
- Secondary leukemia: Secondary acute leukemia may occur (5.8)
- Embryo-fetal toxicity: Can cause fetal harm. Advise of potential risk to a fetus and use of effective contraception. (5.9, 8.1, 8.3)

6 ADVERSE REACTIONS

Common adverse reactions are nephrotoxicity, peripheral neuropathy, nausea and vomiting, myelosuppression, and ototoxicity. (6)

To report SUSPECTED ADVERSE REACTIONS, contact WG Critical Care at 1-866-562-4708 or FDA at 1-800-FDA-1088 or www.fda.gov/medwatch.

8 USE IN SPECIFIC POPULATIONS

- Lactation: Advise not to breastfeed. (8.2)
- Females and Males of Reproductive Potential: Verify pregnancy status prior to initiation of cisplatin for injection. Can impair fertility. (8.3)

FULL PRESCRIBING INFORMATION

WARNING: NEPHROTOXICITY, PERIPHERAL NEUROPATHY, NAUSEA AND VOMITING and MYELOSUPPRESSION.

- Nephrotoxicity: cisplatin for injection can cause severe renal toxicity, including acute renal failure. Severe renal toxicities are dose-related and cumulative. Ensure adequate hydration and monitor renal function and electrolytes. Consider dose reductions or alternative treatments in patients with renal impairment [see Dosage and Administration (2.1) and Warnings and Precautions (5.1)].
- Peripheral Neuropathy: cisplatin for injection can cause dose-related peripheral neuropathy that becomes more severe with repeated courses of the drug [see Warnings and Precautions (5.2)].
- Nausea and Vomiting: cisplatin for injection can cause severe nausea and vomiting. Use highly effective antiemetic premedication [see Dosage and Administration (2.1) and Warnings and Precautions (5.3)].
- Myelosuppression: cisplatin for injection can cause severe myelosuppression with fatalities due to infections. Monitor blood counts accordingly. Interruption of therapy may be required [see Warnings and Precautions (5.4)].

1 INDICATIONS AND USAGE

1.1 Advanced Testicular Cancer

Cisplatin for injection is indicated for the treatment of advanced testicular cancer.

1.2 Advanced Ovarian Cancer

Cisplatin for injection is indicated for the treatment of advanced ovarian cancer.

1.3 Advanced Bladder Cancer

Cisplatin for injection is indicated for the treatment of advanced bladder cancer.

2 DOSAGE AND ADMINISTRATION

2.1 Hydration and Anti-Emetic Treatment

Patients treated with cisplatin for injection must receive appropriate pre-treatment hydration. Maintain adequate hydration and urinary output for 24 hours after cisplatin for injection administration [see Warnings and Precautions (5.1)]. Administer pre-treatment and post-treatment antiemetics as appropriate [see Warnings and Precautions (5.7)].

2.2 Advanced Testicular Cancer

Cisplatin for injection has been administered at 20 mg/m^2 intravenously daily for 5 days per cycle. Other doses and combination regimens have been used.

2.3 Advanced Ovarian Cancer

Cisplatin for injection has been administered at 75 mg/m^2 to 100 mg/m^2 intravenously per cycle once every 3 to 4 weeks on Day 1. Other doses and combination regimens have been used.

2.4 Advanced Bladder Cancer

Cisplatin for injection has been administered at 50 mg/m^2 to 70 mg/m^2 intravenously per cycle once every 3 to 4 weeks. For heavily pretreated patients, an initial dose of 50 mg/m^2 per cycle repeated every 4 weeks is recommended. Other doses and combination in regimens have been used.

2.5 Dose Modifications

Consider alternative treatments or dose reductions for patients with impaired creatinine clearance, myelosuppression, or neuropathy. Consider permanent discontinuation for Grade 3-4 neuropathy. [See Warnings and Precautions (5.1)]

2.6 Preparation, Handling, and Administration

Do not use needles or intravenous sets containing aluminum parts that can come in contact with cisplatin for injection during preparation or administration. Aluminum reacts with cisplatin for injection, causing precipitate formation and a loss of potency.

Cisplatin for injection is a cytotoxic drug. Follow applicable special handling and disposable procedures.^1

Reconstitution

Reconstitute 50 mg vials with 50 mL of Sterile Water for Injection, USP. Each mL of the resulting solution will contain 1 mg of cisplatin for injection. Reconstitution results in a clear or colorless to slight yellow solution. Do not refrigerate the reconstituted solution. Parenteral drug products should be inspected visually for particulate matter and discoloration prior to administration, whenever solution and container permit. The reconstituted solution is stable for 20 hours at controlled room temperature [20°C to 25°C (68°F to 77°F)]. Solution removed from the amber vial should be protected from light if it is not to be used within six hours.

Dilution

For preparation of the infusion solution, it is recommended that the reconstituted solution be further diluted in 1 to 2 L of a compatible infusion solution with or without 37.5 g of mannitol. Refer to detailed references for specific infusion solution stability and compatibility information.

Administration

Administer cisplatin for injection by slow intravenous infusion.

3 DOSAGE FORMS AND STRENGTHS

Cisplatin for injection, USP: single-dose vials containing 50 mg of cisplatin as white to light yellow lyophilized powder for reconstitution.

4 CONTRAINDICATIONS

Cisplatin for injection is contraindicated in patients with severe hypersensitivity to cisplatin [see Warnings and Precautions (5.4)].

5 WARNINGS AND PRECAUTIONS

5.1 Nephrotoxicity

Cisplatin for injectioncan cause dose-related nephrotoxicity, including acute renal failure that becomes more prolonged and severe with repeated courses of the drug. Renal toxicity typically begins during the second week after a dose ofcisplatin for injection. Patients with baseline renal impairment, geriatric patients, patients who are taking other nephrotoxic drugs, or patients who are not well hydrated may be more susceptible to nephrotoxicity [see Use in Specific Populations (8.5, 8.6)].

Ensure adequate hydration before, during, and after cisplatin for injectionadministration [see Dosage and Administration (2.1)]. Measure serum creatinine, blood urea nitrogen, creatinine clearance, and serum electrolytes including magnesium prior to initiating therapy, and as clinically indicated. Consider magnesium supplementation as clinically needed.

Consider alternative treatments or reduce the dose of cisplatin for injection for patients with baseline renal impairment or who develop significant reductions in creatinine clearance during treatment with cisplatin for injection according to clinical treatment guidelines [see Dosage and Administration (2.5)].

5.2 Peripheral Neuropathy

Cisplatin for injectioncan cause dose-related peripheral neuropathy that becomes more severe with repeated courses of the drug. Neurologic symptoms have been reported to occur after a single dose. Neuropathy can also have a delayed onset from 3 to 8 weeks after the last dose of cisplatin for injection. Manifestations include paresthesias in a stocking-glove distribution, areflexia, and loss of proprioception and vibratory sensation. The neuropathy may progress further even after stopping treatment. Peripheral neuropathy may be irreversible in some patients.

Perform a neurological examination before initiating cisplatin for injection, at appropriate intervals during therapy, and after completion of therapy. Consider discontinuation of cisplatin for injection for patients who develop symptomatic peripheral neuropathy. Geriatric patients may be more susceptible to peripheral neuropathy [see Use in Specific Populations (8.5)].

5.3 Nausea and Vomiting

Cisplatin for injection is a highly emetogenic antineoplastic agent. Premedicate with anti-emetic agents [see Dosage and Administration (2.1)]. Without antiemetic therapy, marked nausea and vomiting occur in almost all patients treated with cisplatin for injection and may be so severe that the drug must be discontinued. Nausea and vomiting may begin within 1 to 4 hours after treatment and last up to 72 hours. Maximal intensity occurs 48 to 72 hours after administration. Various degrees of vomiting, nausea, and/or anorexia may persist for up to 1 week after treatment. Delayed nausea and vomiting (begins or persists 24 hours or more after chemotherapy) has occurred in patients attaining complete emetic control on the day of cisplatin for injection therapy. Consider the use of additional anti-emetics following infusion.

5.4 Myelosuppression

Myelosuppression suppression occurs in 25% to 30% of patients treated with cisplatin for injection. Fever and infection have been reported in patients with neutropenia. Potential fatalities due to infection (secondary to myelosuppression) have been reported. Geriatric patients may be more susceptible to myelosuppression [see Use in Specific Populations (8.5)].

Perform standard hematologic tests before initiating cisplatin for injection, before each subsequent course, and as clinically indicated. Closely monitor patients for the development of signs and symptoms of infection during and after treatment with cisplatin for injection. For patients who develop severe myelosuppression during treatment with cisplatin for injection, consider dose modifications and manage according to clinical treatment guidelines.

5.5 Hypersensitivity Reactions

Cisplatin for injection can cause severe hypersensitivity reactions, including anaphylaxis and death. Manifestations have included facial edema, wheezing, tachycardia, and hypotension. Hypersensitivity reactions have occurred within minutes of administration to patients with prior exposure tocisplatin for injection.

Monitor patients receiving cisplatin for injection for possible hypersensitivity reactions. Ensure supportive equipment and medications are available to treat severe hypersensitivity reactions. Severe hypersensitivity reactions require immediate discontinuation of cisplatin for injection and aggressive therapy. Patients with a history of severe hypersensitivity reactions should not be rechallenged with cisplatin for injection [see Contraindications (4)]. Cross-reactivity between platinum-based antineoplastic agents has been reported. Cases of severe hypersensitivity reactions have recurred after rechallenging patients with a different platinum agent.

5.6 Ototoxicity

Cisplatin for injection can cause ototoxicity, which is cumulative and may be severe. Consider audiometric and vestibular function monitoring.

Ototoxicity is manifested by tinnitus, hearing loss in the high frequency range (4,000 to 8,000 Hz) and/or decreased ability to hear normal conversational tones. Ototoxicity can occur during or after treatment and can be unilateral or bilateral. Deafness after the initial dose of cisplatin for injection has been reported. Vestibular toxicity has also been reported.

Ototoxic effects can be more severe and detrimental in pediatric patients, particularly in patients less than 5 years of age. The prevalence of hearing loss in pediatric patients is estimated to be 40-60%. Additional risk factors for ototoxicity include simultaneous cranial irradiation, treatment with other ototoxic drugs and renal impairment. Consider audiometric and vestibular testing in all pediatric patients receiving cisplatin [see Use in Specific Populations (8.4)].

Genetic factors (e.g. variants in the thiopurine S-methyltransferase [TPMT] gene) may also contribute to the cisplatin-induced ototoxicity; although this association has not been consistent across populations and study designs.

5.7 Ocular Toxicity

Optic neuritis, papilledema, and cortical blindness have been reported in patients receiving standard recommended doses ofcisplatin for injection. Blurred vision and altered color perception have been reported after the use of regimens with higher doses and dose frequencies of cisplatin for injection. The altered color perception manifests as a loss of color discrimination, particularly in the blue-yellow axis and irregular retinal pigmentation of the macular area on fundoscopic exam. Improvement and/or total recovery usually occurs after discontinuing cisplatin for injection but can be delayed.

5.8 Secondary Malignancies

The development of acute leukemia secondary to the use of cisplatin for injection has been reported. In these reports, cisplatin for injection was generally given in combination with other leukemogenic agents.

5.9 Embryo-Fetal Toxicity

Based on human data, cisplatin for injection can cause fetal harm when administered to a pregnant woman. Advise pregnant women and females of reproductive potential of the potential risk to a fetus. Advise females of reproductive potential to use effective contraception during treatment and for 14 months after the last dose of cisplatin for injection. Advise male patients with female partners of reproductive potential to use effective contraception during treatment and for 11 months after the last dose of cisplatin for injection [see Use in Specific Populations (8.1, 8.3)].

5.10 Injection Site Reactions

Injection site reactions can occur during the administration of cisplatin for injection. Local soft tissue toxicity has been reported following extravasation of cisplatin for injection. Severity of the local tissue toxicity appears to be related to the concentration of the cisplatin for injection solution. Infusion of solutions with a cisplatin for injection concentration greater than 0.5 mg/mL may result in tissue cellulitis, fibrosis, necrosis, pain, edema, and erythema.

Because of the possibility of extravasation, closely monitor the infusion site during drug administration.

6 ADVERSE REACTIONS

The following adverse reactions are described in greater detail, in other sections:

- Nephrotoxicity [see Warnings and Precautions (5.1)]
- Peripheral Neuropathy [see Warnings and Precautions (5.2)]
- Nausea and vomiting [see Warnings and Precautions (5.3)]
- Myelosuppression [see Warnings and Precautions (5.4)]
- Hypersensitivity reactions [see Warnings and Precautions (5.5)]
- Ototoxicity [see Warnings and Precautions (5.6]
- Ocular toxicity [see Warnings and Precautions (5.7)]
- Secondary malignancies [see Warnings and Precautions (5.8)]
- Injection site reactions [see Warnings and Precautions (5.10)]

Common adverse reactions are nephrotoxicity, peripheral neuropathy, nausea and vomiting myelosuppression, and ototoxicity. The following adverse reactions have been identified from clinical trials or post-marketing surveillance.

Blood and lymphatic system disorders: Coombs‑positive hemolytic anemia. hemolytic uremic syndrome, thrombotic thrombocytopenic purpura

Cardiovasculardisorders: Venous thromboembolism, arterial thromboembolism, myocardial infarction, cerebrovascular accident, thrombotic microangiopathy, cerebral arteritis, pericardial effusion, cardiac failure, ventricular dysfunction, Raynaud’s phenomenon

Eye disorders: Optic neuritis, papilledema, cortical blindness, blurred vision, color blindness, retinal pigmentation

Gastrointestinal disorders: Nausea, vomiting, anorexia, diarrhea, stomatitis, gastrointestinal perforation, pancreatitis, hiccups

General disorders: Asthenia, malaise

Hepatobiliary disorders: Elevations of aminotransferases, lactate dehydrogenase, and bilirubin; hepatic failure

Hypersensitivity: Anaphylaxis, facial edema, wheezing, tachycardia, and hypotension

Local Site Reactions: Tissue cellulitis, fibrosis, necrosis, pain, edema, and erythema

Metabolism and nutrition disorders: Hypomagnesemia, often requiring magnesium supplementation; hyperuricemia, other electrolyte abnormalities (hypocalcemia, hyponatremia, hypokalemia, and hypophosphatemia), Syndrome of Inappropriate Antidiuretic Hormone Excretion (SIADH), dehydration, tumor lysis syndrome, increased serum amylase

Musculoskeletal disorders: Muscle cramps (localized, painful, involuntary skeletal muscle contractions of sudden onset and short duration)

Nervous system disorders: Peripheral neuropathy, Encephalopathy, loss of motor function, loss of taste, leukoencephalopathy, reversible posterior leukoencephalopathy syndrome, progressive multifocal leukoencephalopathy, seizures, Lhermitte’s sign, dorsal column myelopathy, autonomic neuropathy, seizures, involuntary skeletal muscle contractions, tetany (with hypocalcemia and hypomagnesemia)

Ototoxicity: Tinnitus, hearing loss, deafness, vestibular toxicity

Renal and urinary disorders: Nephrotoxicity including renal failure, renal electrolyte wasting, azotemia, decreased creatinine clearance

Respiratory disorders: pneumonitis/interstitial lung disease, pulmonary embolism

Skin and subcutaneous tissue disorders: Alopecia, rash

7 DRUG INTERACTIONS

The following drug interactions are described in other sections:

- Nephrotoxic drugs [see Warnings and Precautions (5.1)]
- Ototoxic drugs [see Warnings and Precautions (5.6)]

8 USE IN SPECIFIC POPULATIONS

8.1 Pregnancy

Risk Summary

Based on human data from published literature, cisplatin for injection can cause fetal harm when administered to pregnant women. Advise pregnant women and females of reproductive potential of the potential risk to a fetus. Data demonstrates transplacental transfer of cisplatin. Exposure of pregnant women to cisplatin-containing chemotherapy has been associated with oligohydramnios, intrauterine growth restriction, and preterm birth. Cases of neonatal acute respiratory distress syndrome, cytopenias, and hearing loss have been reported. Cisplatin for injection administration to animals during and after organogenesis resulted in teratogenicity. A published study in mice showed placental transfer of cisplatin increased with placenta maturation.

The background risk of major birth defects and miscarriage for the indicated populations are unknown. However, the background risk in the U.S. general population of major birth defects is 2-4% and of miscarriage is 15-20% of clinically recognized pregnancies.

8.2 Lactation

Risk Summary

Limited data from published literature report the presence of cisplatin in human milk in low amounts. Because of the potential for serious adverse reactions from cisplatin for injection in a breastfed child and because of the potential for tumorigenicity shown for cisplatin for injection, advise lactating women not to breastfeed during treatment with cisplatin for injection.

8.3 Females and Males of Reproductive Potential

Pregnancy Testing

Verify the pregnancy status of females of reproductive potential prior to initiation of cisplatin for injection.

Contraception

Females

Cisplatin for injection can cause fetal harm when administered to a pregnant woman [see Use in Specific Populations (8.1)]. Advise females of reproductive potential to use effective contraception during treatment and for 14 months following the last dose of cisplatin for injection.

Males

Advise male patients with female partners of reproductive potential to use effective contraception during treatment and for 11 months after the last dose of cisplatin for injection.

Infertility

Females

The use of cisplatin has been associated with cumulative dose-dependent ovarian failure, premature menopause, and reduced fertility.

Males

The use of cisplatin has been associated with a cumulative dose-dependent impairment of spermatogenesis (oligospermia, azoospermia; possibly irreversible) and reduced fertility.

8.4 Pediatric Use

Ototoxic effects may be more severe and detrimental in pediatric patients receiving cisplatin for injection, particularly in patients less than 5 years of age. Consider audiometric and vestibular function monitoring in all patients receiving cisplatin for injection. The prevalence of hearing loss in pediatric patients is particularly high and is estimated to be 40% to 60%.

Earlier detection of hearing loss can limit the potential impact of hearing impairment on a pediatric patient’s cognitive and social development [see Warnings and Precautions (5.6)].

8.5 Geriatric Use

For the treatment of metastatic testicular tumors or advanced bladder cancer, clinical studies of cisplatin for injection did not include sufficient numbers of subjects aged 65 and over to determine whether they respond differently from younger subjects. In four clinical trials of combination chemotherapy for advanced ovarian carcinoma, 1,484 patients received cisplatin either in combination with cyclophosphamide or with paclitaxel. Of these, 426 (29%) were older than 65 years. In these trials, age was not found to be a prognostic factor for survival. However, in a later secondary analysis for one of these trials, geriatric patients were found to have shorter survival compared with younger patients.

In all four trials, geriatric patients experienced more severe neutropenia than did younger patients. Higher incidences of severe thrombocytopenia and leukopenia were also seen in geriatric patients compared with younger patients, although not in all cisplatin-containing treatment arms. In the two trials where nonhematologic toxicity was evaluated according to age, geriatric patients had a numerically higher incidence of peripheral neuropathy than did younger patients. Other reported clinical experience suggests that geriatric patients may be more susceptible to nephrotoxicity, myelosuppression, and infectious complications than are younger patients [see Warnings and Precautions (5.1, 5.2, 5.4)].

Cisplatin is known to be substantially excreted by the kidney. Because elderly patients are more likely to have decreased renal function, care should be taken in dose selection, and renal function should be monitored.

8.6 Use in Patients with Renal Impairment

Patients with baseline renal impairment may be more susceptible to nephrotoxicity [see Warnings and Precautions (5.1)]. Ensure adequate hydration before, during, and after cisplatin for injection administration [see Dosage and Administration (2.1)]. Measure serum creatinine, blood urea nitrogen, creatinine clearance, and serum electrolytes prior to initiating therapy, and as clinically indicated. Consider alternative treatments or reduce the dose of cisplatin for injection for patients with baseline renal impairment or who develop significant reductions in creatinine clearance during treatment with cisplatin for injection according to clinical treatment guidelines [see Dosage and Administration (2.5)].

10 OVERDOSAGE

Acute overdosage with cisplatin for injection may result in renal failure, hepatic failure, hearing loss, ocular toxicity, myelosuppression, nausea and vomiting, and neuritis. In addition, death can occur following overdosage.

Management of overdosage should include general supportive measures to sustain the patient through any period of toxicity that may occur. Important measures include renal protection by intravenous hydration with or without the use of an osmotic diuretic. Hemodialysis is not effective because of the high degree of protein binding of cisplatin for injection. Plasmapheresis has been used to treat cases of cisplatin for injection overdosage, but the optimal treatment regimen has not been established.

For current information on the management of poisoning or overdosage, contact the National Poison Control Center at 1-800-222-1222 or www.poison.org.

11 DESCRIPTION

Cisplatin for injection, USP, a platinum-based drug for intravenous use, is a white to light yellow lyophilized powder. Each vial of Cisplatin for injection, USP contains 50 mg cisplatin, 450 mg Sodium Chloride, USP, and 500 mg Mannitol, USP. Cisplatin for Injection, USP may contain hydrochloric acid for pH adjustment.

Cisplatin, the active ingredient in Cisplatin for injection, USP, is a yellow to orange crystalline powder with the molecular formulaCl2H6N2Pt and a molecular weight of 300.05. Cisplatin is a heavy metal complex containing a central atom of platinum surrounded by two chloride atoms and two ammonia molecules in the cis position. It is soluble in water or saline at 1 mg/mL and in dimethylformamide at 24 mg/mL. It has a melting point of 207°C.

The structural formula is:

12 CLINICAL PHARMACOLOGY

12.1 Mechanism of Action

The main mechanism of the cytotoxic action involves the binding of cisplatin to genomic DNA in the cell nucleus to form interstrand and intrastrand cross-links. This interferes with normal transcription and/or DNA replication mechanisms and triggers cytotoxic processes that lead to cell death.

12.3 Pharmacokinetics

Distribution

Cisplatin dose not undergo the instantaneously and reversible binding to plasma protein that is characteristic of normal drug-protein binding. Platinum from cisplatin, but not cisplatin itself, becomes bound to several plasma proteins, including albumin, transferrin, and gamma globulin. Three hours after a bolus injection and 2 hours after the end of a 3‑hour infusion, 90% of the plasma platinum is protein bound. The complexes between albumin and the platinum from cisplatin do not dissociate to a significant extent and are slowly eliminated with a minimum half-life of 5 days or more.

Following cisplatin doses of 20 mg/m^2 to 120 mg/m^2, platinum is present in tissues for as long as 180 days after the last administration. With the exception of intracerebral tumors, platinum concentrations in tumors are generally somewhat lower than the concentrations in the organ where the tumor is located. Hepatic metastases have the highest platinum concentrations, but these are similar to the platinum concentrations in normal liver. Maximum red blood cell concentrations of platinum are reached within 90 to 150 minutes after a 100 mg/m^2 dose of cisplatin and decline in a biphasic manner with a terminal half-life of 36 to 47 days.

Metabolism

The chlorine atoms of cisplatin are more subject to chemical displacement reactions by nucleophiles, such as water or sulfhydryl groups, than to enzyme-catalyzed metabolism. At physiological pH, the predominant molecular species are cisplatin and monohydroxymonochloro cis-diamine platinum (II) in nearly equal concentrations. The latter, combined with the possible direct displacement of the chlorine atoms by sulfhydryl groups of amino acids or proteins, accounts for the instability of cisplatin in biological matrices. The ratios of cisplatin to total free (ultrafilterable) platinum in the plasma vary considerably between patients and range from 0.5 to 1.1 after a dose of 100 mg/m^2.

Elimination

Over a dose range of 40 mg to 140 mg cisplatin per m^2 given as a bolus injection or as infusions varying in length from 1 hour to 24 hours, from 10% to about 40% of the administered platinum is excreted in the urine in 24 hours. Over 5 days following administration of 40 mg/m^2 to 100 mg/m^2 doses given as rapid, 2‑ to 3‑hour or 6‑ to 8‑hour infusions, a mean of 35% to 51% of the dosed platinum is excreted in the urine. Similar mean urinary recoveries of platinum of about 14% to 30% of the dose are found following 5 daily administrations of 20 mg/m^2 per day, 30 mg/m^2 per day, or 40 mg/m^2 per day. Only a small percentage of the administered platinum is excreted beyond 24 hours post-infusion and most of the platinum excreted in the urine in 24 hours is excreted within the first few hours.

The parent compound, cisplatin, is excreted in the urine and accounts for 13% to 17% of the dose excreted within 1 hour after administration of 50 mg/m^2. The mean renal clearance of cisplatin exceeds creatinine clearance and was 62 mL/min per m^2 and 50 mL/min per m^2 following administration of 100 mg/m^2 as 2‑hour or 6‑ to 7‑hour infusions, respectively.

Plasma concentrations of the parent compound, cisplatin, decrease monoexponentially with a half-life of about 20 to 30 minutes following bolus administrations of 50 mg/m^2 or 100 mg/m^2 doses. Monoexponential decreases and plasma half-lives of about 0.5 hour are also seen following 2‑hour or 7‑hour infusions of 100 mg/m^2. After the latter, the total body clearances and volumes of distribution at steady-state for cisplatin are about 15 Liters per hour per m^2 to 16 Liters per hour per m^2 and 11 Liters per m^2 to 12 Liters per m^2.

The renal clearance of free (ultrafilterable) platinum also exceeds the glomerular filtration rate, indicating that cisplatin or other platinum-containing molecules are actively secreted by the kidneys. The renal clearance of free platinum is nonlinear and variable and is dependent on dose, urine flow rate, and individual variability in the extent of active secretion and possible tubular reabsorption.

No significant relationships exist between the renal clearance of either free platinum or cisplatin and creatinine clearance.

13 NONCLINICAL TOXICOLOGY

13.1 Carcinogenesis, Mutagenesis, Impairment of Fertility

The carcinogenic effect of cisplatin for injection was studied in BDIX rats. Cisplatin for injection was administered three times a week at 1 mg/kg body weight intraperitoneally to 50 BDIX rats for 3 weeks. Four hundred fifty-five days after the first application, 33 animals died, 13 of them related to malignancies (12 leukemias and 1 renal fibrosarcoma) [see Warnings and Precautions (5.8)].

Cisplatin is mutagenic in the bacteria reverse mutation (Ames) test and produces chromosome aberrations in mammalian cells.

15 REFERENCES

1. OSHA Hazardous Drugs. OSHA. http://www.osha.gov/SLTC/hazardousdrugs/index.html

16 HOW SUPPLIED/STORAGE AND HANDLING

How Supplied

Cisplatin for injection, USP

NDC 44567-530-01—Each single-dose amber vial contains 50 mg of cisplatin as a white to light yellow lyophilized powder for reconstitution.

Storage

Store at 20°C to 25°C (68°F to 77°F); excursions permitted to 15°C to 30°C (59°F to 86°F) [see USP Controlled Room Temperature]. Prior to reconstitution, store in original carton to protect from light. Discard unused portion.

Handling and Disposal

Cisplatin for injection, USP is a cytotoxic drug. Follow applicable special handling and disposal procedures.^1

17 PATIENT COUNSELING INFORMATION

Nephrotoxicity

Inform patients that cisplatin for injection can cause nephrotoxicity and that renal function and electrolyte monitoring during treatment is necessary. If indicated, inform patients about the use of electrolyte supplements [see Warnings and Precautions (5.1)].

Peripheral Neuropathy

Advise patients to report any new paresthesias to their healthcare provider [see Warnings and Precautions (5.2)].

Nausea and Vomiting

Advise patients concerning the use of antiemetics to prevent nausea and vomiting and to report persistent or severe symptoms to their healthcare provider [see Warnings and Precautions (5.3)].

Myelosuppression

Advise patients that cisplatin for injection can reduce the absolute neutrophil count and the platelet count resulting in an increased risk of infection and bleeding and to contact their healthcare provider for new onset fever, symptoms of infection, or bleeding [see Warnings and Precautions (5.4)].

Ototoxicity

Advise patients to report any symptoms of hearing loss or vestibular dysfunction to their healthcare provider and that periodic monitoring of hearing may be performed [see Warnings and Precautions (5.6)].

Embryo-Fetal Toxicity

- Advise females of reproductive potential of the potential risk to a fetus and to inform their healthcare provider if they are pregnant or become pregnant [see Warnings and Precautions 5.9 and Use in Specific Populations 8.1)].
- Advise females of reproductive potential to use effective contraception during treatment and for 14 months following the last dose of cisplatin for injection [see Use in Specific Populations (8.3)].
- Advise male patients with female partners of reproductive potential to use effective contraception during treatment and for 11 months following the last dose of cisplatin for injection [see Use in Specific Populations (8.3)].

Lactation

Advise females not to breastfeed during treatment with cisplatin for injection [see Use in Specific Populations (8.2)].

Infertility

Inform patients that treatment with cisplatin for injection may lead to permanent impairment of spermatogenesis, ovarian failure or premature menopause, and reduced fertility in both genders [see Use in Specific Populations (8.3)].

Alopecia

Inform patients that cisplatin for injection can cause alopecia.

Manufactured for:
WG Critical Care, LLC
Paramus, NJ 07652

Made in Italy

PACKAGE/LABEL PRINCIPAL DISPLAY PANEL

CISplatin doses greater than 100 mg/m^2 once every 3 to
4 weeks are rarely used. See Prescribing information.

NDC 44567-530-01 Single-dose vial

Discard unused portion

CISplatin for Injection, USP

For Intravenous Infusion

50 mg per vial Rx only

Caution: Cytotoxic Agent WG Critical Care